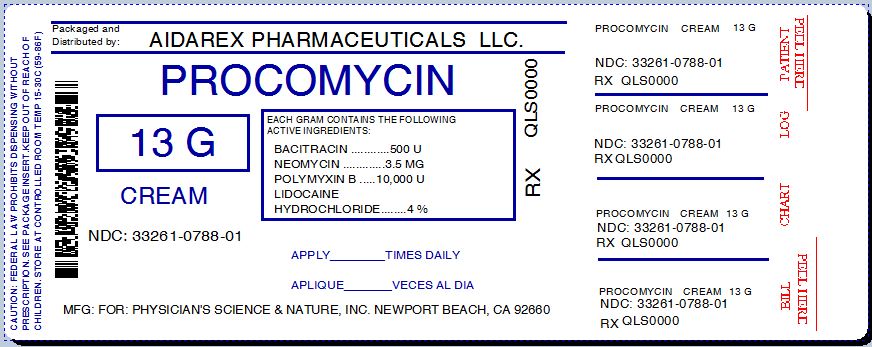 DRUG LABEL: ProCoMycin
NDC: 33261-788 | Form: CREAM
Manufacturer: Aidarex Pharmaceuticals LLC
Category: otc | Type: HUMAN OTC DRUG LABEL
Date: 20140128

ACTIVE INGREDIENTS: BACITRACIN 500 [iU]/1 g; NEOMYCIN 0.0035 g/1 g; POLYMYXIN B 10000 [iU]/1 g; LIDOCAINE HYDROCHLORIDE 0.04 g/1 g
INACTIVE INGREDIENTS: ALLANTOIN; ARACHIDYL ALCOHOL; ARNICA MONTANA FLOWER; ASCORBIC ACID; DOCOSANOL; ALOE VERA LEAF; BENZALKONIUM CHLORIDE; ALKYL (C12-15) BENZOATE; MEDIUM-CHAIN TRIGLYCERIDES; CETOSTEARYL ALCOHOL; CYCLOMETHICONE 5; DIMETHICONE; DIPALMITOYL HYDROXYPROLINE; GLYCERIN; SOYBEAN; SUNFLOWER OIL; METHYLPARABEN; PANTHENOL; PHENOXYETHANOL; PROPYLPARABEN; WATER; SHEA BUTTER

Drug Facts

Active ingredients

Bacitracin 500 units

Neomycin 3.5.mg

Polymyxin B 10,000 units

Purpose

First Aid Antibiotic

Active ingredient

Lidocaine Hydrochloride 4%

Purpose

Local Anesthetic

Uses

- First aid to help prevent the infection in minor cuts, scrapes and burns
- For the temporary relief of pain or itching.

Warnings

For external use only.

Do not use

- in the eyes
- over large areas of the body
- if allergic to any of the ingredients
- longer than 1 week unless directed by a doctor.

Consult a doctor

- if under 2 years of age
- in case of deep cuts or puncture wounds, animal or human bites, or serious burns
- if pregnant or breast feeding.

Stop use and consult a doctor

- if the condition persists or worsens
- if symptoms persist for more than 7 days or clear up and occur again within a few days
- if a rash or other allergic reaction develops.

Keep out of reach of children.

If swallowed, get medical help or contact a Poison Control Center right away.

Directions for use

- Clean the affected area
- apply a small amount of this product (an amount equal to the surface area of the tip of the finger) on the area 3 times daily.
- may be covered with a sterile bandage
- store at controlled room temperature 15°-30° (59°-86°).

Inactive ingredients

acrylates/dimethicone coploymer, allantoin, aloe barbadensis (aloe vera) leaf juice, arachidyl alcohol, arachidyl glucoside, arnica montana flower extract, ascorbic acid (vitamin C), behenyl alcohol, beta-glucan, benzalkonium chloride, beta-glucan, butyrospermum parkii (shea) butter, C 12-15 alkyl benzoate, caprylic/capric triglyceride, cetearyl alcohol, cetearyl glucoside, cyclopentasiloxane, dimethicone, dipalmitoyl hydroxyproline, glycerin, glycine soja (soybean) oil, helianthus annuus (sunflower) seed oil, hydrolyzed mytilus edulis byssus, methylparaben, panthenol, persea gratissima (avocado) oil, phenoxyethanol, polyglyceryl-6 distearate, propylparaben, sclerotium gum, tocopherol, water (aqua)

Manufactured in the USA for:

Physician's Science and Nature, Inc.

220 Newport Center Drive, 11-634,

Newport Beach, CA 92660

www.procomycin.com

Repackaged By:
Aidarex Pharmaceuticals, LLC.
Corona, CA 92880